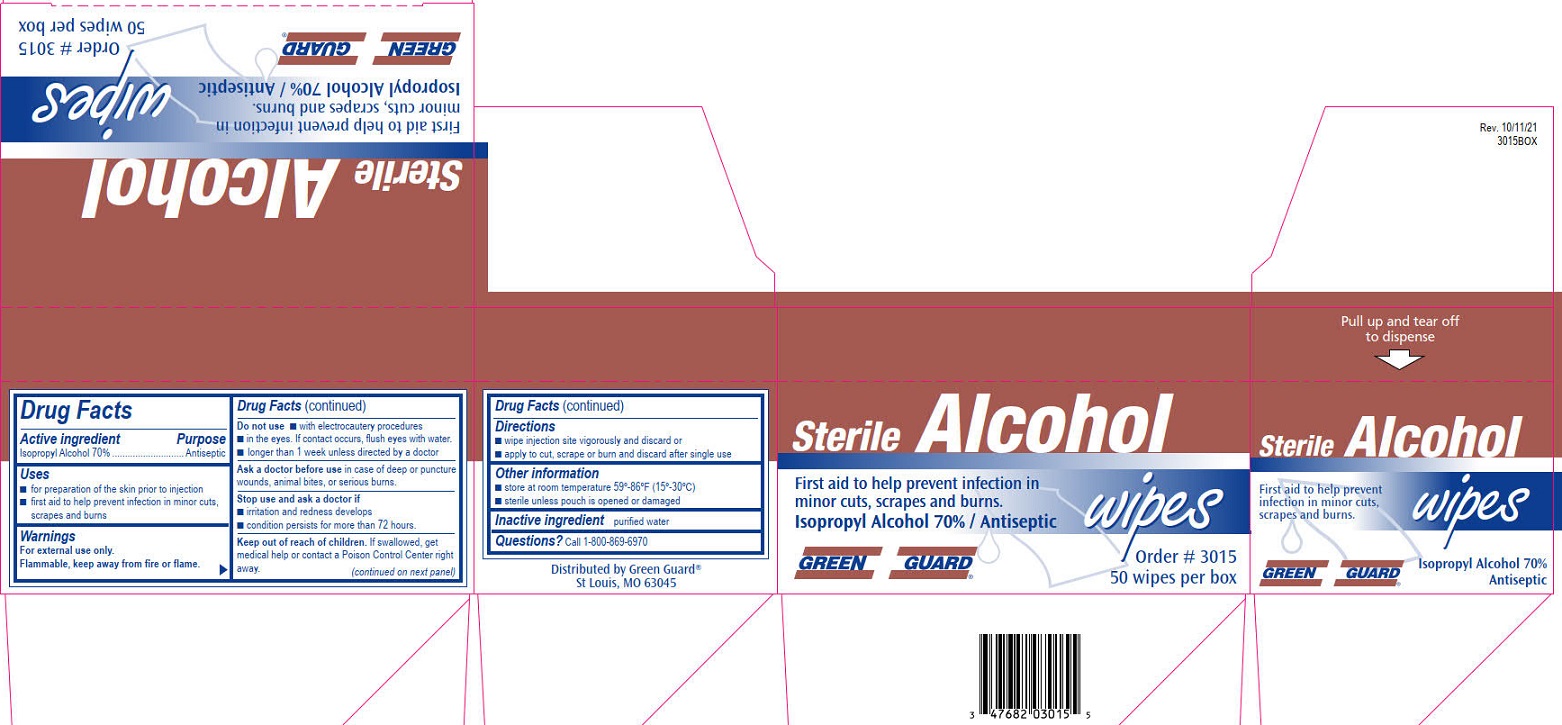 DRUG LABEL: Green Guard Alcohol Wipes
NDC: 47682-299 | Form: CLOTH
Manufacturer: Unifirst First Aid Corporation
Category: otc | Type: HUMAN OTC DRUG LABEL
Date: 20250908

ACTIVE INGREDIENTS: ISOPROPYL ALCOHOL 0.7 mL/1 1
INACTIVE INGREDIENTS: WATER

Green Guard Sterile Alcohol Wipes

Drug Facts

Active ingredient

Isopropyl Alcohol 70%

Purpose

Antiseptic

Uses

- for preparation of the skin prior to injection
- first aid to help prevent infection in minor cuts, scrapes and burns

Warnings

For external use only.

Flammable, keep away from fire or flame.

Do not use

- with electrocautery procedures
- in the eyes. If contact occurs, flush eyes with water.
- longer than 1 week unless directed by a doctor

Ask a doctor before use in case of deep or puncture wounds, animal bites, or serious burns

Stop use and ask a doctor if

- irritation and redness develops
- condition persists for more than 72 hours

Keep out of reach of children.

If swallowed, get medical help or contact a Poison Control Center right away.

Directions

- wipe injection site vigorously and discard or
- apply to cut, scrape or burn and discard after single use

Other information

- store at room temperature 59°-86°F (15°-30°C)
- sterile unless pouch is opened or damaged

Inactive ingredient

purified water

Questions? Call 1-800-869-6870

PACKAGE LABEL

Sterile Alcohol wipes

First aid to help prevent infection in minor cuts,scrapes and burns.

Isopropyl Alcohol 70% / Antiseptic

Green Guard®

Order # 3015

50 wipes per box